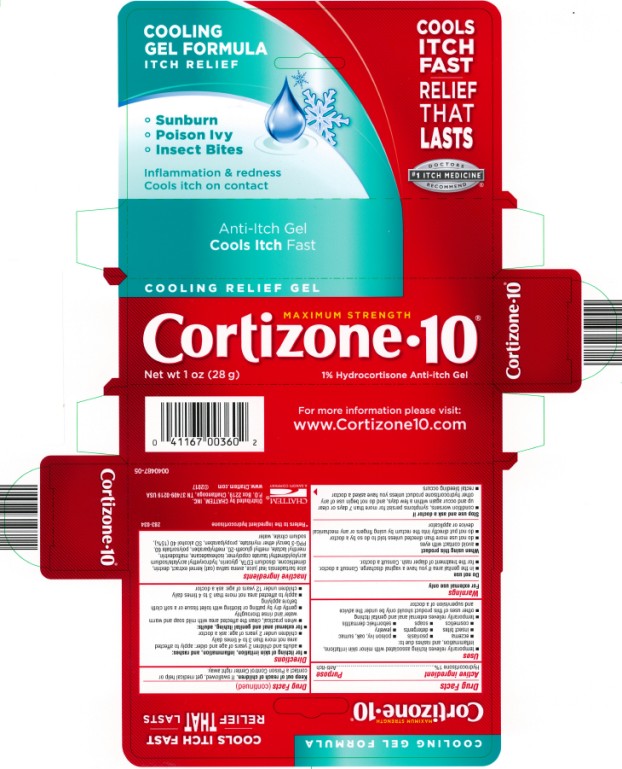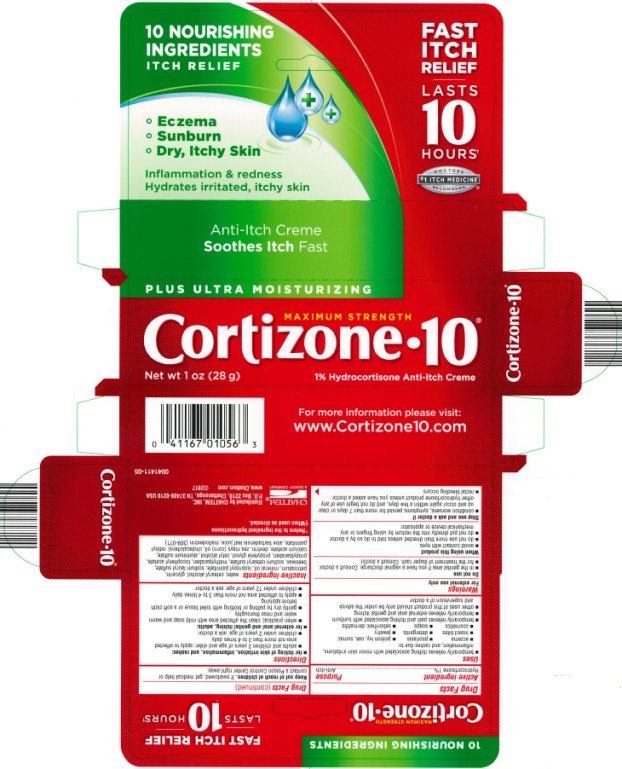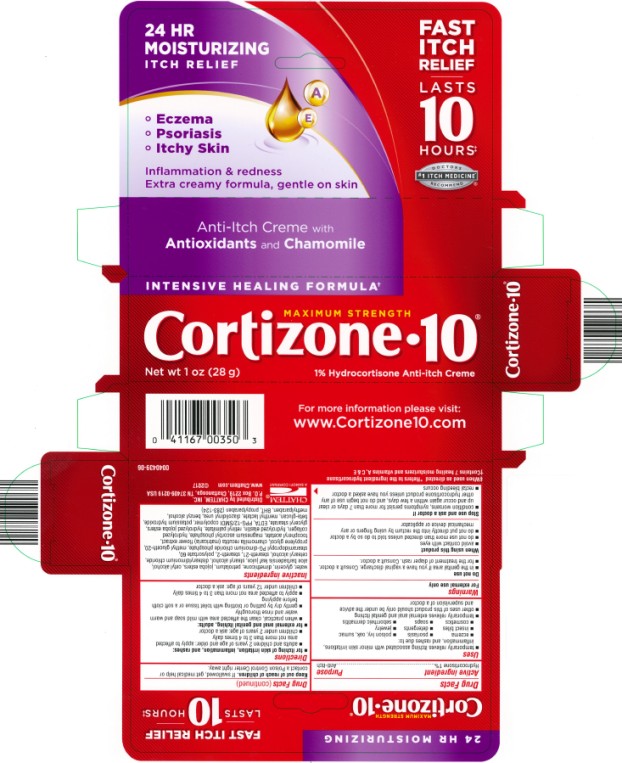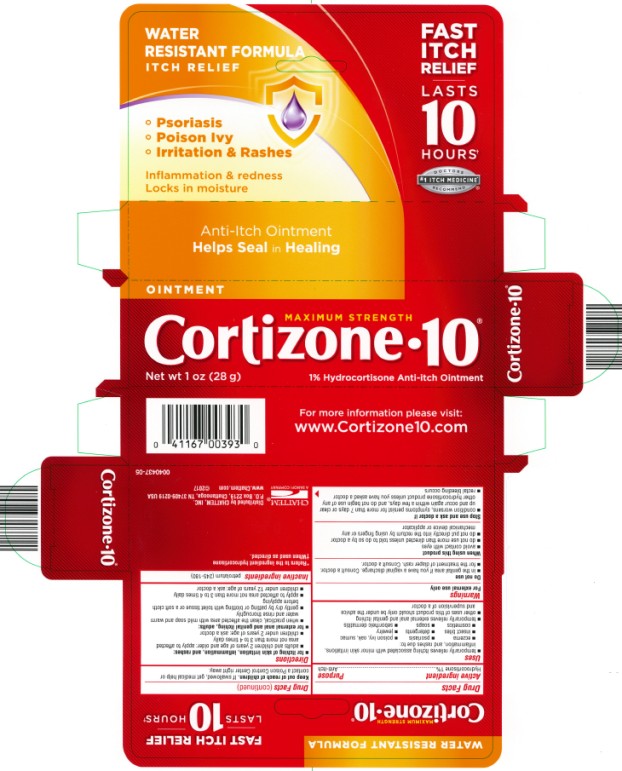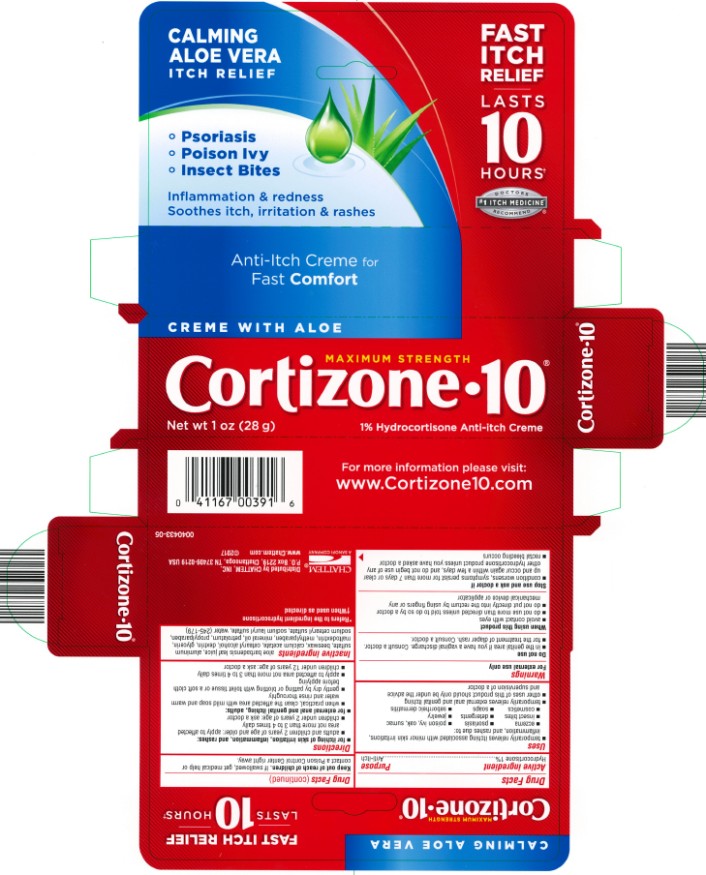 DRUG LABEL: Cortizone 10 Cooling Relief
NDC: 41167-0036 | Form: GEL
Manufacturer: Chattem, Inc.
Category: otc | Type: HUMAN OTC DRUG LABEL
Date: 20251020

ACTIVE INGREDIENTS: HYDROCORTISONE 10 mg/1 g
INACTIVE INGREDIENTS: ALOE VERA LEAF; DIMETHICONE; EDETATE DISODIUM; GLYCERIN; MALTODEXTRIN; METHYLPARABEN; POLYSORBATE 60; PROPYLPARABEN; SODIUM CITRATE; WATER; CYCLOMETHICONE 5; ALCOHOL

Cortizone-10

Active Ingredient:

Hydrocortisone 1%

Purpose

Anti-itch

Uses

- temporarily relieves itching associated with minor skin irritations, inflammation, and rashes due to:
  - eczema
  - psoriasis
  - poison ivy, oak, sumac
  - insect bites
  - detergents
  - jewelry
  - cosmetics
  - soaps
  - seborrheic dermatitis
  - temporarily relieves external anal and genital itching
  - other uses of this product should only be under the advice and supervision of a doctor

Warnings

For external use only

Do not use

- in the genital area if you have a vaginal discharge. Consult a doctor.
- for the treatment of diaper rash. Consult a doctor.

When using this product

- avoid contact with eyes
- do not use more than directed unless told to do so by a doctor
- do not put directly into the rectum by using fingers or any mechanical device or applicator

Stop use and ask a doctor if

- condition worsens, symptoms persist for more than 7 days or clear up and occur again within a few days, and do not begin use of any other hydrocortisone product unless you have asked a doctor
- rectal bleeding occurs

Keep out of reach of children.

If swallowed, get medical help or contact a Poison Control Center right away.

Directions

- for itching of skin irritation, inflammation, and rashes:
  - adults and children 2 years of age and older: apply to affected area not more than 3 to 4 times daily
  - children under 2 years of age: ask a doctor

- for external anal and genital itching, adults:
  - when practical, clean the affected area with mild soap and warm water and rinse thoroughly
  - gently dry by patting or blotting with toilet tissue or a soft cloth before applying
  - apply to affected area not more than 3 to 4 times daily
  - children under 12 years of age: ask a doctor

Other information

- contents filled by weight, not volume

Inactive Ingredients

aloe barbadensis leaf juice, avena sativa (oat) kernel extract, cyclopentasiloxane, dimethicone, dimethicone/vinyl dimethicone crosspolymer, disodium EDTA, glycerin, hydroxyethyl acrylate/sodium acryloyldimethyl taurate copolymer, isohexadecane, maltodextrin, menthyl lactate, methyl gluceth-20, methylparaben, polysorbate 60, propylparaben, SD Alcohol 40-2 (15%), sodium citrate, water

CHATTEM®

*Refers to the ingredient hydrocortisone

Distributed by CHATTEM, INC.
P.O. Box 2219, Chattanooga,
TN 37409-0219 USA ©2008
www.ditchtheitch.com 0042740-02

Cortizone-10® Creme

Active Ingredient:

Hydrocortisone 1%

Purpose

Anti-itch

Uses

- temporarily relieves itching associated with minor skin irritations, inflammation, and rashes due to:
  - eczema
  - psoriasis
  - poison ivy, oak, sumac
  - insect bites
  - detergents
  - jewelry
  - cosmetics
  - soaps
  - seborrheic dermatitis
  - temporarily relieves external anal and genital itching
  - other uses of this product should only be under the advice and supervision of a doctor

Warnings

For external use only

Do not use

- in the genital area if you have a vaginal discharge. Consult a doctor.
- for the treatment of diaper rash. Consult a doctor.

When using this product

- avoid contact with eyes
- do not use more than directed unless told to do so by a doctor.
- do not put directly into the rectum by using fingers or any mechanical device or applicator

Stop use and ask a doctor if

- condition worsens, symptoms persist for more than 7 days or clear up and occur again within a few days, and do not begin use of any other hydrocortisone product unless you have asked a doctor
- rectal bleeding occurs

Keep out of reach of children.

If swallowed, get medical help or contact a Poison Control Center right away.

Directions

- for itching of skin irritation, inflammation, and rashes:
  - adults and children 2 years of age and older: apply to affected area not more than 3 to 4 times daily
  - children under 2 years of age: ask a doctor

- for external anal and genital itching, adults:
  - when practical, clean the affected area with mild soap and warm water and rinse thoroughly
  - gently dry by patting or blotting with toilet tissue or a soft cloth before applying
  - apply to affected area not more than 3 to 4 times daily
  - children under 12 years of age: ask a doctor

Other information

- contents filled by weight, not volume

Inactive Ingredients

aloe barbadensis leaf juice, aluminum sulfate, beeswax, calcium acetate, cetearyl alcohol, dextrin, glycerin, maltodextrin, methylparaben, mineral oil, petrolatum, propylparaben, sodium cetearyl sulfate, sodium lauryl sulfate, water

*Refers to the ingredient hydrocortisone

CHATTEM®

Distributed by CHATTEM, INC.
P.O. Box 2219, Chattanooga,TN 37409-0219 USA ©2008
www.chattem.com 0040433-02

Minor change

Cortizone-10® Creme Intensive Healing Formula

Active Ingredient:

Hydrocortisone 1%

Purpose

Anti-itch

Uses

- temporarily relieves itching associated with minor skin irritations, inflammation, and rashes due to:
  - eczema
  - psoriasis
  - poison ivy, oak, sumac
  - insect bites
  - detergents
  - jewelry
  - cosmetics
  - soaps
  - seborrheic dermatitis
  - temporarily relieves external anal and genital itching
  - other uses of this product should only be under the advice and supervision of a doctor

Warnings

For external use only

Do not use

- in the genital area if you have a vaginal discharge. Consult a doctor.
- for the treatment of diaper rash. Consult a doctor.

When using this product

- avoid contact with eyes
- do not use more than directed unless told to do so by a doctor.
- do not put directly into the rectum by using fingers or any mechanical device or applicator

Stop use and ask a doctor if

- condition worsens, symptoms persist for more than 7 days or clear up and occur again within a few days, and do not begin use of any other hydrocortisone product unless you have asked a doctor
- rectal bleeding occurs

Keep out of reach of children.

If swallowed, get medical help or contact a Poison Control Center right away.

Directions

- for itching of skin irritation, inflammation, and rashes:
  - adults and children 2 years of age and older: apply to affected area not more than 3 to 4 times daily
  - children under 2 years of age: ask a doctor

- for external anal and genital itching, adults:
  - when practical, clean the affected area with mild soap and warm water and rinse thoroughly
  - gently dry by patting or blotting with toilet tissue or a soft cloth before applying
  - apply to affected area not more than 3 to 4 times daily
  - children under 12 years of age: ask a doctor

Other information

- contents filled by weight, not volume

Inactive Ingredients

water, glycerin, dimethicone, petrolatum, jojoba esters, cetyl alcohol, aloe barbadensis leaf juice, stearyl alcohol, distearyldimonium chloride, cetearyl alcohol, steareth-21, steareth-2, polysorbate 60, stearamidopropyl PG-dimonium chloride phosphate, methyl gluceth-20, chamomilla recutita (matricaria) flower extract, tocopheryl acetate, magnesium ascorbyl phosphate, hydrolyzed collagen, hydrolyzed elastin, retinyl palmitate, hydrolyzed jojoba esters, glyceryl stearate, EDTA, PPG-12/SMDI copolymer, potassium hydroxide, avena sativa (oat) kernel extract, menthyl lactate, diazolidinyl urea, benzyl alcohol, methylparaben, BHT, propylparaben

*Refers to the ingredient hydrocortisone
†Contains 7 healing moisturizers and vitamins A, C & E

CHATTEM®

Distributed by CHATTEM, INC.
P.O. Box 2219, Chattanooga,
TN 37409-0219 USA ©2008 0040439-02

Cortizone-10® Ointment

Active Ingredient:

Hydrocortisone 1%

Purpose

Anti-itch

Uses

- temporarily relieves itching associated with minor skin irritations, inflammation, and rashes due to:
  - eczema
  - psoriasis
  - poison ivy, oak, sumac
  - insect bites
  - detergents
  - jewelry
  - cosmetics
  - soaps
  - seborrheic dermatitis
  - temporarily relieves external anal and genital itching
  - other uses of this product should only be under the advice and supervision of a doctor

Warnings

For external use only

Do not use

- in the genital area if you have a vaginal discharge. Consult a doctor.
- for the treatment of diaper rash. Consult a doctor.

When using this product

- avoid contact with eyes
- do not use more than directed unless told to do so by a doctor
- do not put directly into the rectum by using fingers or any mechanical device or applicator

Stop use and ask a doctor if

- condition worsens, symptoms persist for more than 7 days or clear up and occur again within a few days, and do not begin use of any other hydrocortisone product unless you have asked a doctor
- rectal bleeding occurs

Keep out of reach of children.

If swallowed, get medical help or contact a Poison Control Center right away.

Directions

- for itching of skin irritation, inflammation, and rashes:
  - adults and children 2 years of age and older: apply to affected area not more than 3 to 4 times daily
  - children under 2 years of age: ask a doctor

- for external anal and genital itching, adults:
  - when practical, clean the affected area with mild soap and warm water and rinse thoroughly
  - gently dry by patting or blotting with toilet tissue or a soft cloth before applying
  - apply to affected area not more than 3 to 4 times daily
  - children under 12 years of age: ask a doctor

Other information

- contents filled by weight, not volume

Inactive Ingredients

petrolatum

*Refers to the ingredient hydrocortisone

CHATTEM®

Distributed by CHATTEM, INC.
P.O. Box 2219, Chattanooga, TN 37409-0219 USA ©2008
www.chattem.com
0040437-02

Cortizone-10® Plus Creme

Active Ingredient:

Hydrocortisone 1%

Purpose

Anti-itch

Uses

- temporarily relieves itching associated with minor skin irritations, inflammation, and rashes due to:
  - eczema
  - psoriasis
  - poison ivy, oak, sumac
  - insect bites
  - detergents
  - jewelry
  - cosmetics
  - soaps
  - seborrheic dermatitis
  - temporarily relieves external anal and genital itching
  - other uses of this product should only be under the advice and supervision of a doctor

Warnings

For external use only

Do not use

- in the genital area if you have a vaginal discharge. Consult a doctor.
- for the treatment of diaper rash. Consult a doctor.

When using this product

- avoid contact with eyes
- do not use more than directed unless told to do so by a doctor.
- do not put directly into the rectum by using fingers or any mechanical device or applicator

Stop use and ask a doctor if

- condition worsens, symptoms persist for more than 7 days or clear up and occur again within a few days, and do not begin use of any other hydrocortisone product unless you have asked a doctor
- rectal bleeding occurs

Keep out of reach of children.

If swallowed, get medical help or contact a Poison Control Center right away.

Directions

- for itching of skin irritation, inflammation, and rashes:
  - adults and children 2 years of age and older: apply to affected area not more than 3 to 4 times daily
  - children under 2 years of age: ask a doctor

- for external anal and genital itching, adults:
  - when practical, clean the affected area with mild soap and warm water and rinse thoroughly
  - gently dry by patting or blotting with toilet tissue or a soft cloth before applying
  - apply to affected area not more than 3 to 4 times daily
  - children under 12 years of age: ask a doctor

Other information

- contents filled by weight, not volume

Inactive Ingredients

aloe barbadensis leaf juice, aluminum sulfate, beeswax, calcium acetate, cetearyl alcohol, cetyl alcohol, cholecalciferol, dextrin, glycerin, isopropyl palmitate, maltodextrin, methylparaben, mineral oil, petrolatum, propylene glycol, propylparaben, retinyl palmitate, sodium cetearyl sulfate, sodium lauryl sulfate, tocopheryl acetate, water, zea mays (corn) oil

*Refers to the ingredient hydrocortisone

CHATTEM®

Distributed by CHATTEM, INC.
P.O. Box 2219, Chattanooga,TN 37409-0219 USA ©2008
www.chattem.com 0040435-02

Principal Display Panel

Cooling
gel formula
itch relief
Cools
Itch
Fast
relief
that
lasts

- Sunburn
- Poison Ivy
- Insect Bites

Inflammation and redness
Cools itch on Contact
MAXIMUM STRENGTH
Cortizone-10®
COOLING RELIEF GEL
Net wt 1oz (28g) 1% Hydrocortisone Anti-Itch Gel

Principal Display Panel

10 Nourishing
Ingredients
Itch relief
Fast
Itch
Lasts
10
Hours

- Eczema
- Sunburn
- Dry, Itchy Skin

Inflammation & redness
Hydrates irritated, itchy skin
PLUS ULTRA MOISTURIZING
MAXIMUM STRENGTH
Cortizone-10®
Net wt 1oz (28g) 1% Hydrocortisone Anti-Itch CREME

Principal Display Panel

Fast
Itch
Relief
Lasts
10
Hours
24 HOURS
MOISTURIZING
Itch Relief

- Eczema
- Psoriasis
- Itchy Skin

Inflammation & redness
Extra creamy formula, gentle on skin
INTENSIVE HEALING FORMULA†
MAXIMUM STRENGTH
Cortizone-10®
Net wt 1oz (28g) 1% Hydrocortisone Anti-Itch Crème

Principal Display Panel

Fast
Itch
Relief
Last
10
Hours
Water
Resistant Formula
Itch Relief

- Psoriasis
- Poison Ivy
- Irritation & Rashes

Inflammation & redness
Locks in moisture
Anti – Itch Ointment
Helps Seal in Healing
DOCTORS
#1 ITCH MEDICINE*TM
RECOMMEND
THE ITCH MEDICINE DOCTORS RECOMMEND*
MAXIMUM STRENGTH
Cortizone-10®
Net wt 1oz (28g) 1% Hydrocortisone Anti-Itch OINTMENT

Principal Display Panel

Fast
Itch
Relief
Last
10
Hours
Calming
Aloe Vera
Itch Relief

- Psoriasis
- Poison Ivy
- Insect Bites

Inflammation & redness
Soothes itch, irritation & rashes
DOCTORS
#1 ITCH MEDICINE*TM
RECOMMEND
MAXIMUM STRENGTH
Cortizone-10® plus
Net wt 1oz (28g) 1% Hydrocortisone Anti-Itch CREME